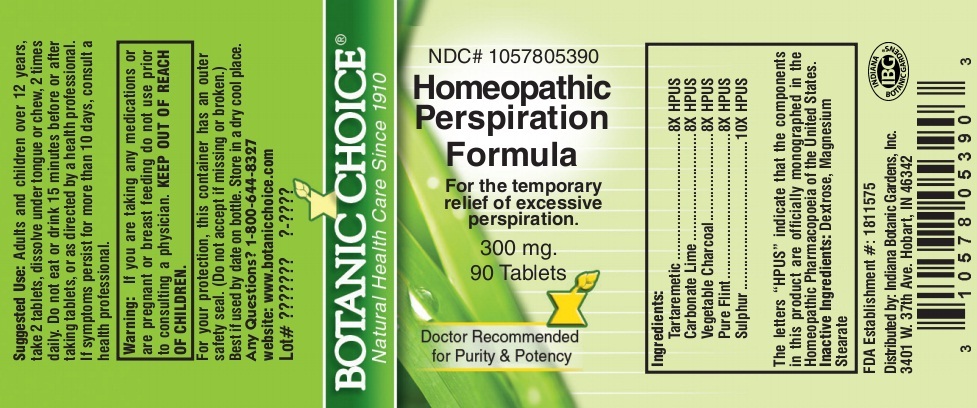 DRUG LABEL: Homeopathic Perspiration Formula
NDC: 10578-053 | Form: TABLET
Manufacturer: Indiana Botanic Gardens
Category: homeopathic | Type: HUMAN OTC DRUG LABEL
Date: 20140401

ACTIVE INGREDIENTS: ANTIMONY POTASSIUM TARTRATE 8 [hp_X]/1 1; OYSTER SHELL CALCIUM CARBONATE, CRUDE 8 [hp_X]/1 1; ACTIVATED CHARCOAL 8 [hp_X]/1 1; SILICON DIOXIDE 8 [hp_X]/1 1; SULFUR 10 [hp_X]/1 1
INACTIVE INGREDIENTS: DEXTROSE; MAGNESIUM STEARATE

Homeopathic Perspiration Formula

Suggested Use:

Adults and children over 12 years, take 2 tablets, dissolve under tongue or chew, 2 times daily. Do not eat or drink 15 minutes before or after taking tablets, or as directed by a health professional.

STOP USE

If symptoms persist for more than 10 days, consult a health professional.

Warning:

If you are taking any medications or are pregnant or breast feeding do not use prior to consulting a physician.

KEEP OUT OF REACH OF CHILDREN.

For your protection, this container has an outer safety seal. (Do not accept if missing or broken.)

Best if used by date on bottle. Store in a dry cool place.

Any Questions? 1-800-644-8327

website: www.botanicchoice.com

INDICATIONS AND USAGE

For the temporary relief of excessive perspiration.

PURPOSE

For the temporary relief of excessive perspiration.

Ingredients:

Tartaremetic .................................8X HPUS

Carbonate Lime ............................8X HPUS

Vegetable Charcoal .......................8X HPUS

Pure Flint ......................................8X HPUS

Sulphur .......................................10X HPUS

The letters "HPUS" indicate that the components in this product are officially monographed in the Homeopathic Pharmacopoeia of the United States.

Inactive Ingredients:

Dextrose, Magnesium Stearate

FDA Establishment #: 1811575

Distributed by: Indiana Botanic Gardens, Inc.

3401 W. 37th Ave. Hobart, IN 46342

Botanic Choice

Natural Health Care Since 1910

NDC# 1057805390

Homeopathic Perspiration Formula

For the temporary relief of excessive perspiration.

300 mg.

90 Tablets